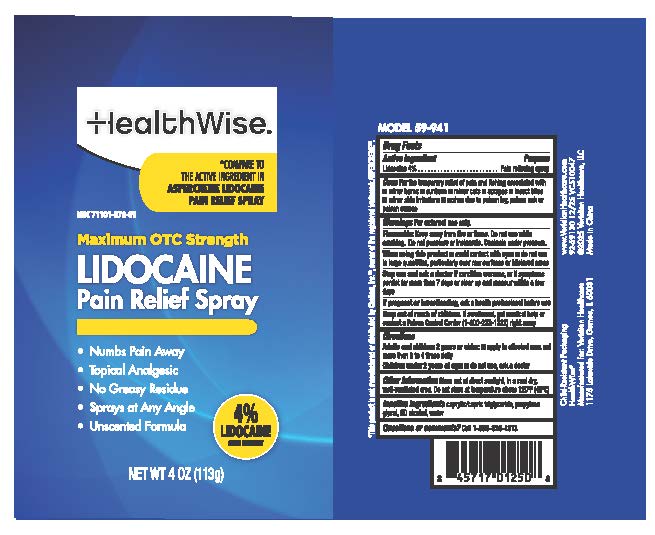 DRUG LABEL: HealthWise Maximum Pain Relief
NDC: 71101-078 | Form: SPRAY
Manufacturer: Veridian Healthcare
Category: otc | Type: HUMAN OTC DRUG LABEL
Date: 20251217

ACTIVE INGREDIENTS: LIDOCAINE 4 g/100 mL
INACTIVE INGREDIENTS: ALCOHOL 95%; PROPYLENE GLYCOL; CAPRYLIC/CAPRIC TRIGLYCERIDE

HealthWise Maximum OTC Strength Lidocaine Pain Relief

Drug Facts

Lidocaine

PURPOSE

Pain relieving spray

Uses

first aid to help prevent bacterial contamination or skin infection, and for temporary relief of pain and itching associated with:

- minor burns
- sunburn
- minor cuts
- scrapes
- insect bites
- minor skin irritations
- rashes due to poison ivy, poison oak or poison sumac

Warnings

For external use only

Flammable Keep away from fire or flame. Do not use while smoking. Do not punture or incinerate. Contents under pressure.

Stop use and ask a doctor

- skin irritation develops
- condition worsens
- symptoms persist for more than 7 days or clear up and occur again withing a few days

When using this product

- avoid contact with eyes
- do not use in large quantities, particularly over raw surfaces or blistered areas

Stop use and ask a doctor if

- skin irritation develops
- condition worsens, or symptoms persist for more than 7 days symptoms or clear up and occur again within a few days

Keep out of reach of children.If swallowed, get medical help or contact a Poison Control Center (1-800-222-1222) right away.

Directions

- adults and children 2 years and older:apply to affected area not more than 3 to 4 times daily.
- children under 2 years of age:do not use, ask a doctor

Other information

- Store out of direct sunlight, in a cool dry well-ventilated area
- Do not store at temperature above 120F (49C)

Inactive ingredients

caprylic/capric triglyceride, propylene glycol, SD alcohol